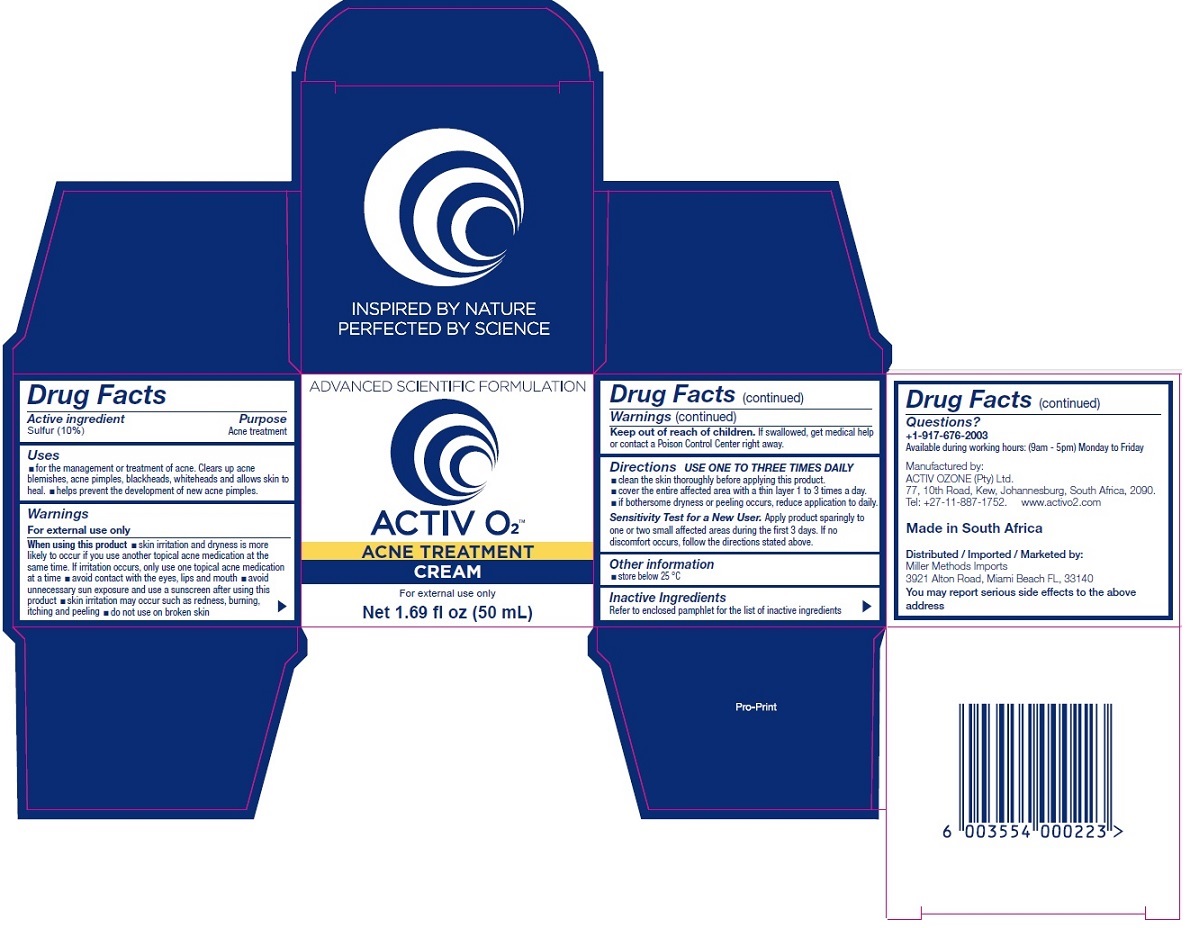 DRUG LABEL: Activ O2 Acne Treatment Cream
NDC: 71577-222 | Form: CREAM
Manufacturer: Activ Ozone (pty) Ltd
Category: otc | Type: HUMAN OTC DRUG LABEL
Date: 20170919

ACTIVE INGREDIENTS: SULFUR 10 g/100 mL
INACTIVE INGREDIENTS: CETOSTEARYL ALCOHOL; EDETATE DISODIUM ANHYDROUS; ETHYLHEXYL COCOATE; JOJOBA OIL; OLIVE OIL; PHENOXYETHANOL; POLYSORBATE 20; POTASSIUM CETYL PHOSPHATE; PPG-3 BENZYL ETHER MYRISTATE; SODIUM POLYACRYLATE (8000 MW); WATER

ACTIV O2 ACNE TREATMENT CREAM

Active ingredient

Sulfur (10%)

Purpose

Acne treatment

Uses

•for the management or treatment of acne. Clears up acne blemishes, acne pimples, blackheads, whiteheads and allows skin to heal. •helps prevent the development of new acne pimples.

Warnings

For external use only

When using this product •skin irritation and dryness is more likely to occur if you use another topical acne medication at the same time. If irritation occurs, only use one topical acne medication at a time •avoid contact with the eyes, lips and mouth •avoid unnecessary sun exposure and use a sunscreen after using this product •skin irritation may occur such as redness, burning, itching and peeling •do not use on broken skin

Keep out of reach of children. If swallowed, get medical help or contact a Poison Control Center right away.

Directions

USE ONE TO THREE TIMES DAILY

- clean the skin thoroughly before applying this product.
- cover the entire affected area with a thin layer 1 to 3 times a day.
- if bothersome dryness or peeling occurs, reduce application to daily.

Sensitivity Test for a New User. Apply product sparingly to one or two small affected areas during the first 3 days. If no discomfort occurs, follow the directions stated above.

Inactive Ingredients

Cetearyl Alcohol, Disodium EDTA, Ethylhexyl Cocoate, Fragrance (Parfum), Jojoba (Simmondsia Chinensis) Seed Oil, Olive (Olea Europaea) Fruit Oil, Phenoxyethanol, Polysorbate 20, Potassium Cetyl Phosphate, PPG-3 Benzyl Ether Myristate, Sodium Polyacrylate, Water (Aqua)

Other information

• store below 25 °C

Questions?

+1-917-676-2003

Available during working hours: (9am - 5pm) Monday to Friday

Manufactured by:
ACTIV OZONE (Pty) Ltd.
77, 10th Road, Kew, Johannesburg, South Africa, 2090.
Tel: +27-11-887-1752. www.activo2.com

Made in South Africa

Distributed / Imported / Marketed by:
Miller Methods Imports
3921 Alton Road, Miami Beach FL, 33140

You may report serious side effects to the above address

INSPIRED BY NATURE

PERFECTED BY SCIENCE

ADVANCED SCIENTIFIC FORMULATION